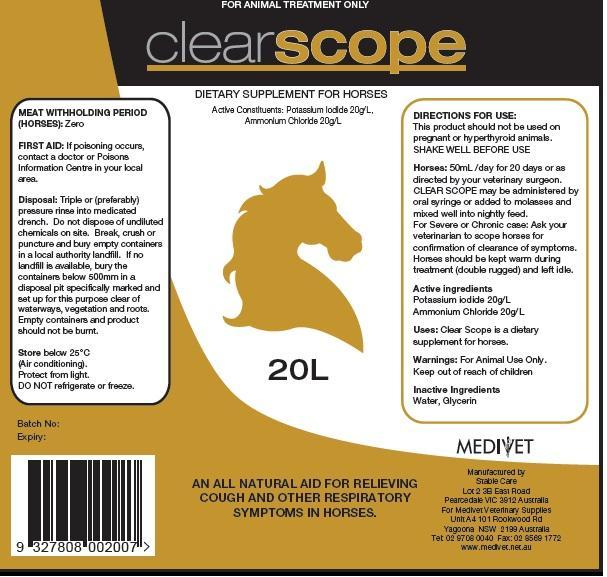 DRUG LABEL: Clear Scope
NDC: 51083-106 | Form: SOLUTION
Manufacturer: Medivet Pty Ltd
Category: animal | Type: OTC ANIMAL DRUG LABEL
Date: 20121129

ACTIVE INGREDIENTS: POTASSIUM IODIDE 20 g/1 L; AMMONIUM CHLORIDE 20 g/1 L
INACTIVE INGREDIENTS: WATER; GLYCERIN

Directions For Use

DOSAGE AND ADMINISTRATION

This product should not be used on pregnant or hyperthyroid animals.

SHAKE WELL BEFORE USE
Horses: 50mL /day for 20 days or as directed by your veterinary surgeon.

CLEAR SCOPE may be administered by oral syringe or added to molasses and mixed well into nightly feed.For Severe or Chronic case: Ask your
veterinarian to scope horses for confirmation of clearance of symptoms.Horses should be kept warm during treatment (double rugged) and left idle.

Active Ingredients

Potassium Iodide 20 g/L

Ammonium Chloride 20 g/L

Uses

Clear Cough is a dietary supplement for horses.

Warnings

For Animal Use only.

Inactive Ingredients

Water and Glycerin.

Keep Out of reach of Children

PACKAGE LABEL

Manufactured By :

Stable Care

Lot 2 3B East Road

Pearcedale VIC 3912 Australia

Manufactured For

Medivet Veterinary Supplies

U4A 101 Rook Wood RD,

Yagoona, NSW 2199, Australia

Meat Withholding Period (Horses): Zero

FIRST AID: If poisoning occurs,contact a doctor or Poisons Information Centre in your local area.
Disposal: Triple or (preferably)pressure rinse into medicated drench. Do not dispose of undiluted
chemicals on site. Break, crush or puncture and bury empty containers in a local authority landfill. If no land fill is available, bury the containers below 500 mm in a disposal pit specifically marked and set up for this purpose clear of waterways, vegetation and roots.Empty containers and product should not be burnt.

Store below 25°C
(Air conditioning).
Protect from light.
DO NOT refrigerate or freeze